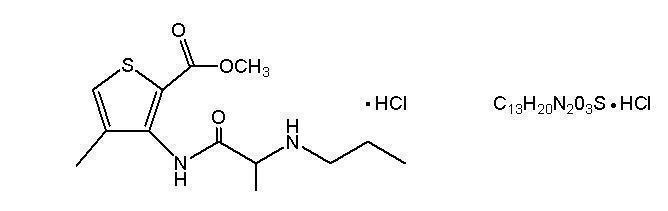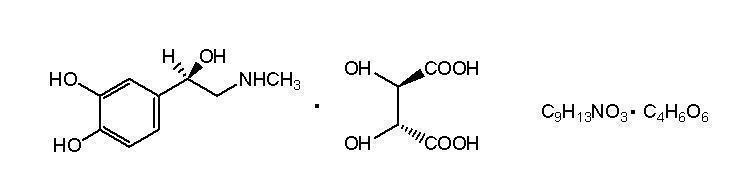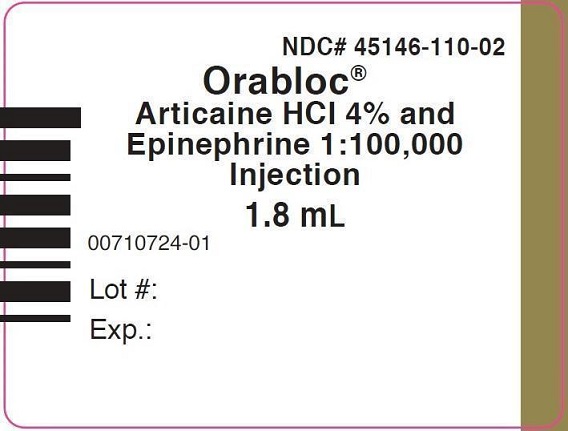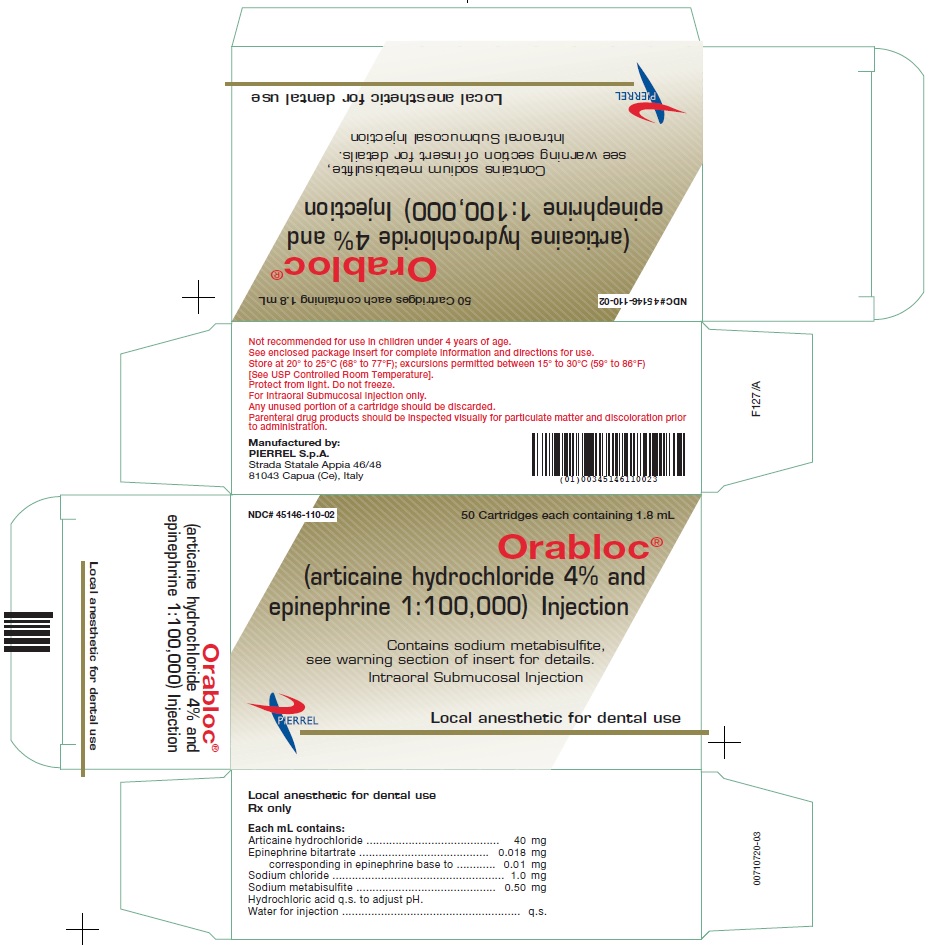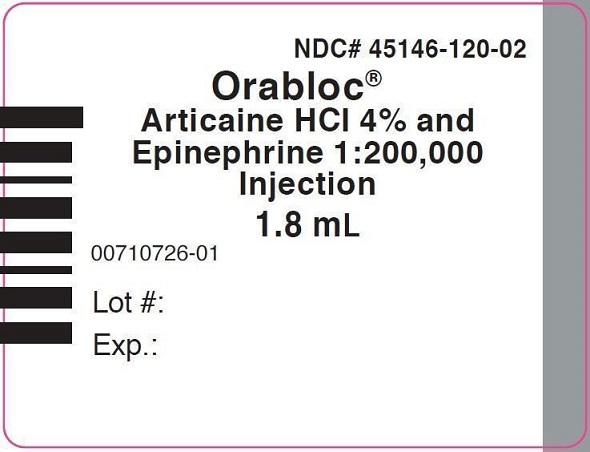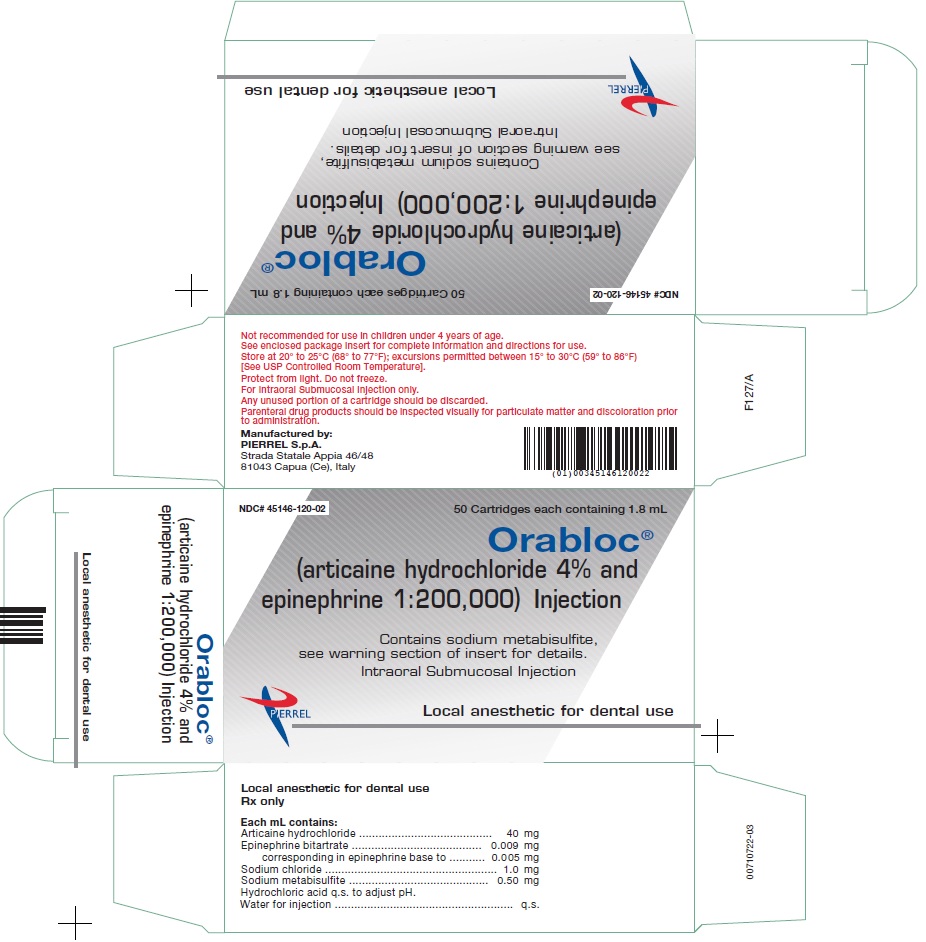 DRUG LABEL: Orabloc
NDC: 45146-110 | Form: INJECTION
Manufacturer: Pierrel S.p.A.
Category: prescription | Type: HUMAN PRESCRIPTION DRUG LABEL
Date: 20181122

ACTIVE INGREDIENTS: ARTICAINE HYDROCHLORIDE 40 mg/1 mL; EPINEPHRINE BITARTRATE 10 ug/1 mL

HIGHLIGHTS OF PRESCRIBING INFORMATION

These highlights do not include all the information needed to use ORABLOC® safely and effectively. See full prescribing information for ORABLOC®.
ORABLOC® (articaine HCl and epinephrine) injection, for intraoral submucosal infiltration use
Initial U.S. Approval: 2000

RECENT MAJOR CHANGES

Warnings and Precautions, Methemoglobinemia (5.4) 11/2018

1 INDICATIONS AND USAGE

ORABLOC is a combination of articaine HCl, an amide local anesthetic, and epinephrine, a vasoconstrictor, indicated for local, infiltrative, or conductive anesthesia in both simple and complex dental procedures in adults and pediatric patients 4 years of age and older (1).

2 DOSAGE AND ADMINISTRATION

- For dental procedures by intraoral submucosal infiltration or nerve block (2.1):
  - For infiltration: 0.5 mL-2.5 mL (20 mg-100 mg articaine HCl) (2.1)
  - For nerve block: 0.5 mL-3.4 mL (20 mg-136 mg articaine HCl) (2.1)
  - For oral surgery: 1 ml-5.1 mL (40 mg-204 mg articaine HCl) (2.1)
- For most routine dental procedures, ORABLOC containing epinephrine 1:200,000 is preferred. However, when more pronounced homeostasis or improved visualization of the surgical field are required, ORABLOC containing epinephrine 1:100,000 may be used. (2.1)
- Maximum recommended dosages (2.2):
  - Healthy adults: 7 mg/kg of articaine HCl and 0.0017mg/kg of epinephrine (equivalent to 0.175 mL/kg for either product presentation, articaine HCl and epinephrine 1:100,000 or 1:200,000)
  - Pediatric patients 4-16 years: 7 mg/kg of articaine HCl and 0.0017mg/kg of epinephrine (equivalent to 0.175 mL/kg for either product presentation, articaine HCl and epinephrine 1:100,000 or 1:200,000)

3 DOSAGE FORMS AND STRENGTHS

Injection provided in glass cartridges (single-dose) containing:

- Articaine hydrochloride 4% (40 mg/mL) and epinephrine 1:200,000 (as epinephrine bitartrate 0.009 mg/mL) (3)
- Articaine hydrochloride 4% (40 mg/mL) and epinephrine 1:100,000 (as epinephrine bitartrate 0.018 mg/mL) (3)

4 CONTRAINDICATIONS

Known hypersensitivity to sulfite (4)

5 WARNINGS AND PRECAUTIONS

Accidental Intravascular Injection: May be associated with convulsions followed by coma and respiratory arrest. Resuscitative equipment, oxygen and other resuscitative drugs should be available. (5.1)
Systemic Toxicity: Systemic absorption of ORABLOC can produce effects on the central nervous and cardiovascular systems. (5.2)
Vasoconstrictor Toxicity: Local anesthetic solutions like ORABLOC that contain a vasoconstrictor should be used cautiously, especially in patients with impaired cardiovascular function or vascular disease. (5.3)
Methemoglobinemia: Cases of methemoglobinemia have been reported in association with local anesthetic use. (5.4)

6 ADVERSE REACTIONS

The most common adverse reactions (incidence >2%) are headache and pain (6.1).
To report SUSPECTED ADVERSE REACTIONS, contact Pierrel S.p.A. at 610-989-4213 or FDA at 1-800-FDA-1088 or www.fda.gov/medwatch.

7 DRUG INTERACTIONS

Monoamine Oxidase Inhibitors, Nonselective Beta-adrenergic Antagonists, or Tricyclic Antidepressants: May produce severe, prolonged hypertension (7)
Phenothiazines and butyrophenones: May reduce or reverse the pressor effect of epinephrine (7)

8 USE IN SPECIFIC POPULATIONS

Pregnancy: Based on animal studies, may cause fetal harm (8.1)
Nursing Mothers: Exercise caution when administering to a nursing woman (8.3)
Pediatric Use: Safety and effectiveness in pediatric patients below the age of 4 years have not been established (8.4)

FULL PRESCRIBING INFORMATION

1 INDICATIONS AND USAGE

ORABLOC is indicated for local, infiltrative, or conductive anesthesia in both simple and complex dental procedures in adults and pediatric patients 4 years of age and older.

2 DOSAGE AND ADMINISTRATION

2.1 General Dosing Information

Table 1 summarizes the recommended dosages of ORABLOC administered by intraoral submucosal infiltration or nerve block for various types of anesthetic dental procedures in healthy adults and pediatric patients.

Table 1: Recommended Dosages for Both Strengths
Procedure | Orabloc Injection; Volume (mL) | Total dose of articaine HCl (mg)
Infiltration | 0.5 mL to 2.5 mL | 20 mg to 100 mg
Nerve block | 0.5 mL to 3.4 mL | 20 mg to 136 mg
Oral surgery | 1 mL to 5.1 mL | 40 mg to 204 mg

The recommended dosages of ORABLOC in healthy adults serve only as a guide to the amount of anesthetic required for most routine dental procedures. The dosage to be used in adults depend on several factors such as type and extent of surgical procedure, depth of anesthesia, degree of muscular relaxation, and condition of the patient. In all cases, administer the lowest dosage that will produce the desired result.

The dosages of ORABLOC to be used in pediatric patients aged 4 to 16 years old are determined by the age and weight of the patient and the type of dental procedure.

For most routine dental procedures, ORABLOC containing epinephrine 1:200,000 is preferred. However, when more pronounced hemostasis or improved visualization of the surgical field are required, ORABLOC containing epinephrine 1:100,000 may be used.

The onset of anesthesia and the duration of anesthesia are proportional to the dosage of the local anesthetic used. Exercise caution when employing large volumes because the incidence of adverse reactions may be dose-related.

2.2 Maximum Recommended Dosages

- Healthy Adults: The maximum dosage of ORABLOC is 7 mg/kg of articaine and 0.0017mg/kg of epinephrine (equivalent to 0.175 mL/kg for either product presentation, articaine HCl and 1:100,000 or 1:200,000 epinephrine).
- Pediatric Patients Ages 4 to 16 Years: The maximum dosage of ORABLOC is 7 mg/kg of articaine and 0.0017mg/kg of epinephrine (equivalent to 0.175 mL/kg for either product presentation, articaine HCl and 1:100,000 or 1:200,000 epinephrine) [see Use in Specific Populations (8.4)].

2.3 Dosing in Special Populations

Lower dosages or dosage reduction may be required in debilitated patients, acutely ill patients, elderly patients, and pediatric patients commensurate with their age and physical condition. No studies have been performed in patients with renal or liver impairment. Exercise caution when using ORABLOC in patients with severe liver disease. [see Warnings and Precautions (5.2), Use in Specific Populations (8.4, 8.5, and 8.6)]

2.4 Important Administration Instructions

Visually inspect ORABLOC for particulate matter and discoloration prior to administration.

ORABLOC (articaine HCl and epinephrine) Injection is available in glass cartridges. Prior to using the glass cartridges, disinfect by wiping the cap thoroughly with USP isopropyl alcohol (70%). Avoid use of isopropyl alcohol, as well as solutions of ethyl alcohol that are not of USP grade because they may contain denaturants that are injurious to rubber. Immersion is not recommended.

3 DOSAGE FORMS AND STRENGTHS

Injection (clear colorless solution), provided in glass cartridges (single-dose) containing (less than a full cartridge or more than one cartridge can be used for an individual patient):

- Articaine hydrochloride 4% (40 mg/mL) and epinephrine 1:200,000 (as epinephrine bitartrate 0.009 mg/mL)
- Articaine hydrochloride 4% (40 mg/mL) and epinephrine 1:100,000 (as epinephrine bitartrate 0.018 mg/mL)

4 CONTRAINDICATIONS

ORABLOC is contraindicated in patients who are hypersensitive to products containing sulfites. Products containing sulfites may cause allergic-type reactions including anaphylactic symptoms and life-threatening or less severe asthmatic episodes in certain susceptible people. Sulfite sensitivity is seen more frequently in asthmatic than in non-asthmatic people [see Warnings and Precautions (5.5)].

5 WARNINGS AND PRECAUTIONS

5.1 Accidental Intravascular Injection

Accidental intravascular injection of ORABLOC may be associated with convulsions, followed by central nervous system or cardiorespiratory depression and coma, progressing ultimately to respiratory arrest. Dental practitioners who employ local anesthetic agents including ORABLOC should be well versed in diagnosis and management of emergencies that may arise from their use. Resuscitative equipment, oxygen, and other resuscitative drugs should be available for immediate use. To avoid intravascular injection, aspiration should be performed before ORABLOC is injected. The needle must be repositioned until no return of blood can be elicited by aspiration. Note, however, that the absence of blood in the syringe does not guarantee that intravascular injection has been avoided.

Small doses of local anesthetics injected in dental blocks may produce adverse reactions similar to systemic toxicity seen with unintentional intravascular injections of larger doses. Confusion, convulsions, respiratory depression and/or respiratory arrest, and cardiovascular stimulation or depression have been reported. These reactions may be due to intra-arterial injection of the local anesthetic with retrograde flow to the cerebral circulation. Patients receiving these blocks should be observed constantly. Resuscitative equipment and personnel for treating adverse reactions should be immediately available. Dosage recommendations should not be exceeded [see Dosage and Administration (2.1)].

5.2 Systemic Toxicity

This includes toxicity arising from accidental intravascular injection of ORABLOC discussed in Section 5.1, as well as that related to higher systemic concentrations of local anesthetics or epinephrine [see Warnings and Precautions (5.3)]. Systemic absorption of local anesthetics including ORABLOC can produce effects on the central nervous and cardiovascular systems.

At blood concentrations achieved with therapeutic doses of ORABLOC, changes in cardiac conduction, excitability, refractoriness, contractility, and peripheral vascular resistance are minimal. However, toxic blood concentrations of ORABLOC can depress cardiac conduction and excitability, which may lead to atrioventricular block, ventricular arrhythmias, and cardiac arrest, possibly resulting in fatalities. In addition, myocardial contractility is depressed and peripheral vasodilatation occurs, leading to decreased cardiac output and arterial blood pressure. ORABLOC should also be used with caution in patients with heart block as well as those with impaired cardiovascular function since they may be less able to compensate for functional changes associated with the prolongation of A-V conduction produced by these drugs.

Restlessness, anxiety, tinnitus, dizziness, blurred vision, tremors, depression, or drowsiness may be early warning signs of central nervous system toxicity.

Careful and constant monitoring of cardiovascular and respiratory (adequacy of ventilation) vital signs and the patient’s state of consciousness should be performed after each local anesthetic injection of ORABLOC. Repeated doses of ORABLOC may cause significant increases in blood levels because of possible accumulation of the drug or its metabolites. The lowest dosage that results in effective anesthesia should be used to decrease the risk of high plasma levels and serious adverse effects. Tolerance to elevated blood levels varies with the status of the patient. Resuscitative equipment, oxygen, and other resuscitative drugs should be available for immediate use. Precautions for epinephrine administration, discussed in Section 5.3 should be observed.

Debilitated patients, elderly patients, acutely ill patients, and pediatric patients should be given reduced doses commensurate with their age and physical condition [see Dosage and Administration (2.1, 2.3)]. No studies have been performed in patients with liver dysfunction, and caution should be used in patients with severe hepatic disease.

5.3 Vasoconstrictor Toxicity

ORABLOC contains epinephrine, a vasoconstrictor that can cause local or systemic toxicity and should be used cautiously. Local toxicity may include ischemic injury or necrosis, which may be related to vascular spasm. ORABLOC should be used with caution in patients during or following the administration of potent general anesthetic agents, since cardiac arrhythmias may occur under such conditions. Patients with peripheral vascular disease and those with hypertensive vascular disease may exhibit exaggerated vasoconstrictor response.

The American Heart Association has made the following recommendation regarding the use of local anesthetics with vasoconstrictors in patients with ischemic heart disease: “Vasoconstrictor agents should be used in local anesthesia solutions during dental practice only when it is clear that the procedure will be shortened or the analgesia rendered more profound. When a vasoconstrictor is indicated, extreme care should be taken to avoid intravascular injection. The minimum possible amount of vasoconstrictor should be used.” (Kaplan, 1986). It is essential to aspirate before any injection to avoid administration of the drug into the blood stream.

5.4 Methemoglobinemia

Cases of methemoglobinemia have been reported in association with local anesthetic use. Although all patients are at risk for methemoglobinemia, patients with glucose-6-phosphate dehydrogenase deficiency, congenital or idiopathic methemoglobinemia, cardiac or pulmonary compromise, infants under 6 months of age, and concurrent exposure to oxidizing agents or their metabolites are more susceptible to developing clinical manifestations of the condition. If local anesthetics must be used in these patients, close monitoring for symptoms and signs of methemoglobinemia is recommended.

Signs of methemoglobinemia may occur immediately or may be delayed some hours after exposure, and are characterized by a cyanotic skin discoloration and/or abnormal coloration of the blood. Methemoglobin levels may continue to rise; therefore, immediate treatment is required to avert more serious central nervous system and cardiovascular adverse effects, including seizures, coma, arrhythmias, and death. Discontinue ORABLOC and any other oxidizing agents. Depending on the severity of the signs and symptoms, patients may respond to supportive care, i.e., oxygen therapy, hydration. A more severe clinical presentation may require treatment with methylene blue, exchange transfusion, or hyperbaric oxygen.

5.5 Anaphylaxis and Allergic-Type Reactions

ORABLOC contains sodium metabisulfite, a sulfite that may cause allergic-type reactions including anaphylactic symptoms and life-threatening or less severe asthmatic episodes in certain susceptible people. The overall prevalence of sulfite sensitivity in the general population is unknown. Sulfite sensitivity is seen more frequently in asthmatic than in non-asthmatic people.

6 ADVERSE REACTIONS

Reactions to articaine are characteristic of those associated with other amide local anesthetics. Adverse reactions to this group of drugs may also result from excessive plasma levels (which may be due to overdosage, unintentional intravascular injection, or slow metabolic degradation), injection technique, volume of injection, or hypersensitivity or they may be idiosyncratic.

6.1 Clinical Studies Experience

Because clinical trials are conducted under widely varying conditions, adverse reaction rates observed cannot be directly compared to rates in other clinical trials and may not reflect the rates observed in practice.

The reported adverse events are derived from clinical trials in the United States and the United Kingdom with a similar product containing articaine and epinephrine. Table 2 displays the adverse events reported in clinical trials where 882 individuals were exposed to articaine containing epinephrine 1:100,000. Table 3 displays the adverse events reported in clinical trials where 182 individuals were exposed to articaine containing epinephrine 1:100,000 and 179 individuals were exposed to articaine containing epinephrine 1:200,000.

Adverse reactions observed in at least 1% of patients:

Table 2: Adverse Reactions in Controlled Trials with an Incidence of 1% or Greater in Patients Administered articaine containing epinephrine 1:100,000
Body System/Reaction | articaine containing epinephrine 1:100,000 (N=882) Incidence
Body as a whole
Face edema | 13 (1%)
Headache | 31 (4%)
Infection | 10 (1%)
Pain | 114 (13%)
Digestive system
Gingivitis | 13 (1%)
Nervous system
Paresthesia | 11 (1%)

Table 3: Adverse Reactions in Controlled Trials with an Incidence of 1% or Greater in Patients Administered articaine containing epinephrine 1:200,000 and articaine containing epinephrine 1:100,000
Reaction | articaine with epinephrine 1:200,000 (N=179) Incidence | articaine with epinephrine 1:100,000 (N=182) Incidence
Any adverse event | 33 (18%) | 35 (19%)
Pain | 11 (6.1%) | 14 (7.6%)
Headache | 9 (5%) | 6 (3.2%)
Positive blood aspiration into syringe | 3 (1.6%) | 6 (3.2%)
Swelling | 3 (1.6%) | 5 (2.7%)
Trismus | 1 (0.3%) | 3 (1.6%)
Nausea and emesis | 3 (1.6%) | 0 (0%)
Sleepiness | 2 (1.1%) | 1 (0.5%)
Numbness and tingling | 1 (0.5%) | 2 (1.%)
Palpitation | 0 (0%) | 2 (1.%)
Ear symptoms (earache, otitis media) | 1 (0.5%) | 2 (1.%)
Cough, persistent cough | 0 (0%) | 2 (1.%)

Adverse reactions observed in less than 1% of patients:

Table 4: Adverse Reactions in Controlled Trials with an Incidence of Less than 1% but Considered Clinically Relevant
Body System | Events
Body as a Whole | Asthenia; back pain; injection site pain; burning sensation above injection site; malaise; neck pain
Cardiovascular System | Hemorrhage; migraine; syncope; tachycardia; elevated blood pressure
Digestive System | Dyspepsia; glossitis; gum hemorrhage; mouth ulceration; nausea; stomatitis; tongue edemas; tooth disorder; vomiting
Hemic and Lymphatic System | Ecchymosis; lymphadenopathy
Metabolic and Nutritional System | Edema; thirst
Musculoskeletal System | Arthralgia; myalgia; osteomyelitis
Nervous System | Dizziness; dry mouth; facial paralysis; hyperesthesia; increased salivation; nervousness; neuropathy; paresthesia; somnolence; exacerbation of Kearns-Sayre Syndrome
Respiratory System | Pharyngitis; rhinitis; sinus pain; sinus congestion
Skin and Appendages | Pruritus; skin disorder
Special Senses | Ear pain; taste perversion

6.2 Postmarketing Experience

The following adverse reactions have been identified during post-approval use of articaine hydrochloride with epinephrine. Because these reactions are reported voluntarily from a population of uncertain size, it is not always possible to reliably estimate their frequency or establish a causal relationship to drug exposure.

Persistent paresthesias of the lips, tongue, and oral tissues have been reported with use of articaine hydrochloride, with slow, incomplete, or no recovery. These postmarketing events have been reported chiefly following nerve blocks in the mandible and have involved the trigeminal nerve and its branches.

Hypoesthesia has been reported with use of articaine, especially in pediatric age groups, which is usually reversible. Prolonged numbness can result in soft tissue injuries such as that of the lips and tongue in these age groups.

Ischemic injury and necrosis has been described following use of articaine with epinephrine and has been postulated to be due to vascular spasm of terminal arterial branches.

Paralysis of ocular muscles has been reported, especially after posterior, superior alveolar injections of articaine during dental anesthesia. Symptoms include diplopia, mydriasis, ptosis and difficulty in abduction of the affected eye. These symptoms have been described as developing immediately after injection of the anesthetic solution and persisting one minute to several hours, with generally complete recovery.

7 DRUG INTERACTIONS

The administration of local anesthetic solutions containing epinephrine to patients receiving monoamine oxidase inhibitors, nonselective beta-adrenergic antagonists or tricyclic antidepressants may produce severe, prolonged hypertension. Phenothiazines and butyrophenones may reduce or reverse the pressor effect of epinephrine. Concurrent use of these agents should generally be avoided. In situations when concurrent therapy is necessary, careful patient monitoring is essential [see Warnings and Precautions (5.1)].

Patients who are administered local anesthetics are at increased risk of developing methemoglobinemia when concurrently exposed to the following drugs, which could include other local anesthetics:

Table 5: Examples of Drugs Associated with Methemoglobinemia:
Class | Examples
Nitrates/Nitrites | nitric oxide, nitroglycerin, nitroprusside, nitrous oxide
Local anesthetics | articaine, benzocaine, bupivacaine, lidocaine, mepivacaine, prilocaine, ropivacaine, procaine, tetracaine
Antineoplastic agents | cyclophosphamide, flutamide, hydroxyurea, ifosfamide, rasburicase
Antibiotics | dapsone, nitrofurantoin, para-aminosalicylic acid, sulfonamides
Antimalarials | chloroquine, primaquine
Anticonvulsants | phenobarbital, phenytoin, sodium valproate,
Other drugs | acetaminophen, metoclopramide, quinine, sulfasalazine

8 USE IN SPECIFIC POPULATIONS

8.1 Pregnancy

Teratogenic Effects-Pregnancy Category C.
There are no adequate and well-controlled studies in pregnant women with articaine with epinephrine. Articaine hydrochloride and epinephrine (1:100,000) has been shown to increase fetal deaths and skeletal variations in rabbits when given in doses approximately 4 times the maximum recommended human dose (MRHD). ORABLOC should be used during pregnancy only if the potential benefit justifies the potential risk to the fetus.

In embryo-fetal toxicity studies in rabbits, 80 mg/kg, subcutaneously (approximately 4 times the MRHD based on body surface area) caused fetal death and increased fetal skeletal variations, but these effects may be attributable to severe maternal toxicity, including seizures, observed at this dose. In contrast, no embryo-fetal toxicities were observed when articaine and epinephrine (1:100,000) was administered subcutaneously throughout organogenesis at doses up to 40 mg/kg in rabbits and 80 mg/kg in rats (approximately 2 times the MRHD based on body surface area).

In pre- and postnatal developmental studies subcutaneous administration of articaine hydrochloride to pregnant rats throughout gestation and lactation, at a dose of 80 mg/kg (approximately 2 times the MRHD based on body surface area) increased the number of stillbirths and adversely affected passive avoidance, a measure of learning, in pups. This dose also produced severe maternal toxicity in some animals. A dose of 40 mg/kg (approximately equal to the MRHD on a mg/m2 basis) did not produce these effects. A similar study using articaine and epinephrine (1:100,000) rather than articaine hydrochloride alone produced maternal toxicity, but no effects on offspring.

8.3 Nursing Mothers

It is not known whether ORABLOC is excreted in human milk. Because many drugs are excreted in human milk, caution should be exercised when ORABLOC is administered to a nursing woman. When using ORABLOC, nursing mothers may choose to pump and discard breast milk for approximately 4 hours (based on plasma half-life) following an injection of ORABLOC (to minimize infant ingestion) and then resume breastfeeding.

8.4 Pediatric Use

Safety and effectiveness of ORABLOC in pediatric patients below the age of 4 years have not been established. Safety of doses greater than 7 mg/kg (0.175 mL/kg) in pediatric patients has not been established.

The safety and effectiveness of ORABLOC for local, infiltrative, or conductive anesthesia in both simple and complex dental procedures have been established in pediatric patients ages 4 to 16 years old. Safety and effectiveness was established in clinical trials with 61 pediatric patients between the ages of 4 and 16 years administered another product containing articaine hydrochloride 4% and epinephrine 1:100,000 injections. Fifty-one of these patients received doses from 0.76 mg/kg to 5.65 mg/kg (0.9 mL to 5.1 mL) of articaine HCl for simple dental procedures and 10 patients received doses between 0.37 mg/kg and 7.48 mg/kg (0.7 mL to 3.9 mL) of articaine HCl for complex dental procedures. Approximately 13% of these pediatric patients required additional injections of anesthetic for complete anesthesia. Safety of doses greater than 7 mg/kg (0.175 mL/kg) of articaine HCl in pediatric patients has not been established. Dosages in pediatric patients should be reduced, commensurate with age, body weight, and physical condition [see Dosage and Administration (2.2)].

8.5 Geriatric Use

In clinical trials, 54 patients between the ages of 65 and 75 years, and 11 patients 75 years and over received another product containing articaine and epinephrine 1:100,000. Among all patients between 65 and 75 years, doses from 0.43 mg/kg to 4.76 mg/kg (0.9 mL to 11.9 mL) of articaine HCl were administered safely to 35 patients for simple procedures and doses from 1.05 mg/kg to 4.27 mg/kg (1.3 mL to 6.8 mL) of articaine HCl were administered safely to 19 patients for complex procedures. Among the 11 patients ≥ 75 years old, doses from 0.78 mg/kg to 4.76 mg/kg (1.3 mL to 11.9 mL) of articaine HCl were administered safely to 7 patients for simple procedures and doses of 1.12 mg/kg to 2.17 mg/kg (1.3 mL to 5.1 mL) of articaine HCl were safely administered to 4 patients for complex procedures.

Approximately 6% of patients between the ages of 65 and 75 years and none of the 11 patients 75 years of age or older required additional injections of anesthetic for complete anesthesia compared with 11% of patients between 17 and 65 years old who required additional injections.

No overall differences in safety or effectiveness were observed between elderly subjects and younger subjects, and other reported clinical experience has not identified differences in responses between the elderly and younger patients, but greater sensitivity of some older individuals cannot be ruled out.

8.6 Renal and Hepatic Impairment

No studies have been performed with articaine hydrochloride 4% and epinephrine 1:200,000 injection or articaine hydrochloride 4% and epinephrine 1:100,000 injection in patients with renal or hepatic dysfunction [see Warnings and Precautions (5.2)].

10 OVERDOSAGE

Acute emergencies from local anesthetics are generally related to high plasma levels encountered during therapeutic use of local anesthetics or to unintended subarachnoid injection of local anesthetic solution [see Warnings and Precautions (5.1, 5.2)].

The first consideration is prevention, best accomplished by careful and constant monitoring of cardiovascular and respiratory vital signs and the patient’s state of consciousness after each local anesthetic injection. At the first sign of change, oxygen should be administered.

The first step in the management of convulsions, as well as hypo-ventilation, consists of immediate attention to the maintenance of a patent airway and assisted or controlled ventilation as needed. The adequacy of the circulation should be assessed. Should convulsions persist despite adequate respiratory support, treatment with appropriate anticonvulsant therapy is indicated. The practitioner should be familiar with the use of anticonvulsant drugs, prior to the use of local anesthetics. Supportive treatment of circulatory depression may require administration of intravenous fluids and, when appropriate, a vasopressor.

If not treated immediately, both convulsions and cardiovascular depression can result in hypoxia, acidosis, bradycardia, arrhythmias, and/or cardiac arrest. If cardiac arrest should occur, standard cardiopulmonary resuscitative measures should be instituted.

For additional information about overdose treatment, call a poison control center (1-800-222-1222).

11 DESCRIPTION

ORABLOC® (articaine hydrochloride and epinephrine injection), for intraoral submucosal infiltration use, is a sterile, aqueous solution that contains articaine HCl 4% (40mg/mL) and epinephrine bitartrate in an epinephrine 1:200,000 or epinephrine 1:100,000 strength.

Articaine HCl is an amino amide local anesthetic, chemically designated as 4-methyl-3-[2-(propylamino)- propionamido]-2-thiophene-carboxylic acid, methyl ester hydrochloride and is a racemic mixture. Articaine HCl has a molecular weight of 320.84 and the following structural formula:

Articaine HCl has a partition coefficient in n-octanol/Soerensen buffer (pH 7.35) of 17 and a pKa of 7.8.

Epinephrine bitartrate, (-)-1-(3,4-dihydroxyphenyl)-2-methylamino-ethanol (+) tartrate (1:1) salt, is a vasoconstrictor with a concentration of 1:200,000 or 1:100,000 (expressed as free base). It has a molecular weight of 333.3 and the following structural formula:

ORABLOC® contains the following inactive ingredients: sodium chloride (1.0 mg/mL), sodium metabisulfite (0.5 mg/mL), and water for injection. The product is formulated with a 10% overage of epinephrine. The pH is adjusted to 3.6 with hydrochloric acid.

12 CLINICAL PHARMACOLOGY

12.1 Mechanism of Action

Articaine HCl is an amide local anesthetic. Local anesthetics block the generation and conduction of nerve impulses, presumably by increasing the threshold for electrical excitation in the nerve, by slowing the propagation of the nerve impulse and by reducing the rate of rise of the action potential. In general, the progression of anesthesia is related to the diameter, myelination, and conduction velocity of the affected nerve fibers. Epinephrine is a vasoconstrictor added to articaine HCl to slow absorption into the general circulation and thus prolong maintenance of an active tissue concentration.

12.2 Pharmacodynamics

Clinically, the order of loss of nerve function is as follows: (1) pain; (2) temperature; (3) touch; (4) proprioception; and (5) skeletal muscle tone. The onset of anesthesia has been shown to be within 1 to 9 minutes of injection of ORABLOC. Complete anesthesia lasts approximately 1 hour for infiltrations and up to approximately 2 hours for nerve block.

Administration of ORABLOC results in a 3- to 5-fold increase in plasma epinephrine concentrations compared to baseline; however, in healthy adults it does not appear to be associated with marked increases in blood pressure or heart rate, except in the case of accidental intravascular injection [see Warnings and Precautions (5.1)].

12.3 Pharmacokinetics

Absorption
Following dental injection by the submucosal route of an articaine solution containing epinephrine 1:200,000, articaine reaches peak blood concentration about 25 minutes after a single dose injection and 48 minutes after three doses. Peak plasma levels of articaine achieved after 68 mg and 204 mg doses are 385 ng/mL and 900 ng/mL, respectively. Following intraoral administration of a near maximum dose of 476 mg, articaine reaches peak blood concentrations of 2037 ng/mL and 2145 ng/mL for articaine solution containing epinephrine 1:100,000 and 1:200,000, respectively, approximately 22 minutes post-dose.

Distribution
Approximately 60% to 80% of articaine HCl is bound to human serum albumin and γ -globulins at 37°C in vitro.

Elimination

Metabolism: Articaine HCl is metabolized by plasma carboxyesterase to its primary metabolite, articainic acid, which is inactive. In vitro studies show that the human liver microsome P450 isoenzyme system metabolizes approximately 5% to 10% of available articaine with nearly quantitative conversion to articainic acid.

Excretion: At the dose of 476 mg of articaine, the elimination half-life was 43.8 minutes and 44.4 minutes for articaine solution containing epinephrine 1:100,000 and 1:200,000, respectively. Articaine is excreted primarily through urine with 53% to 57% of the administered dose eliminated in the first 24 hours following submucosal administration. Articainic acid is the primary metabolite in urine. A minor metabolite, articainic acid glucuronide, is also excreted in urine. Articaine constitutes only 2% of the total dose excreted in urine.

13 NONCLINICAL TOXICOLOGY

13.1 Carcinogenesis, Mutagenesis, Impairment of Fertility

Studies to evaluate the carcinogenic potential of articaine HCI in animals have not been conducted. Five standard mutagenicity tests, including three in vitro tests (the nonmammalian Ames test, the mammalian Chinese hamster ovary chromosomal aberration test, and a mammalian gene mutation test with articaine HCl) and two in vivo mouse micronucleus tests (one with articaine and epinephrine 1:100,000 and one with articaine HCl alone) showed no mutagenic effects.

No effects on male or female fertility were observed in rats for articaine and epinephrine 1:100,000 administered subcutaneously in doses up to 80 mg/kg/day (approximately 2 times the MRHD based on body surface area).

14 CLINICAL STUDIES

Another product containing articaine with epinephrine 1:100,000 was studied in three randomized, double-blind, active-controlled trials to evaluate the effectiveness of articaine containing epinephrine 1:100,000 as a dental anesthetic. Patients ranging in age from 4 years to over 65 years old underwent simple dental procedures such as single uncomplicated extractions, routine operative procedures, single apical resections, and single crown procedures, or complex dental procedures such as multiple extractions, multiple crowns and/or bridge procedures, multiple apical resections, alveolectomies, muco-gingival operations, and other surgical procedures on the bone. Articaine containing epinephrine 1:100,000 was administered by intraoral submucosal infiltration for these dental procedures.

Efficacy was measured immediately following the procedure by having the patient and investigator rate the patient’s procedural pain using a 10 cm visual analog scale (VAS), in which a score of zero represented no pain and a score of 10 represented the worst pain imaginable. Mean patient and investigator VAS pain scores were 0.3 cm-0.4 cm for simple procedures and 0.5 cm-0.6 cm for complex procedures.

Articaine with epinephrine 1:100,000 was also studied compared to articaine with epinephrine 1:200,000 in four randomized, double-blind, active controlled trials. The first two studies used electric pulp testers (EPT) to evaluate the success rate (maximum EPT value within 10 minutes), onset, and duration of articaine containing epinephrine 1:100,000 versus articaine containing epinephrine 1:200,000 and articaine solution without epinephrine in healthy adults between 18 and 65 years old. Results indicated that the anesthetic characteristics of the 1:100,000 and 1:200,000 formulations were not significantly different.

A third study compared the difference in visualization of the surgical field after administration of articaine containing 1:100,000 epinephrine versus articaine containing 1:200,000 epinephrine during bilateral maxillary periodontal surgeries in patients ranging from 21 to 65 years old. Articaine containing 1:100,000 epinephrine provided better visualization of the surgical field and less blood loss during the procedures. In a fourth study, designed to assess and compare cardiovascular safety, when the maximum dose of each formulation was administered, no clinically relevant differences in blood pressure or heart rate between formulations were observed.

15 REFERENCES

Kaplan, EL, editor. Cardiovascular disease in dental practice. Dallas; American Heart Association; 1986.

16 HOW SUPPLIED/STORAGE AND HANDLING

STORAGE AND HANDLING

ORABLOC® (articaine hydrochloride and epinephrine) injection is a clear, colorless solution available in 1.8 mL single-dose glass cartridges, packaged in boxes of 50 and 100 cartridges in the following two strengths (less than a full cartridge or more than one cartridge may be used for an individual patient):

- Articaine HCl 4% (40 mg/mL) and epinephrine 1:200,000 (as epinephrine bitartrate 0.09 mg/mL):
  - NDC 45146-120-02 (50 cartridges/box)
  - NDC 45146-120-01 (100 cartridges/box)
- Articaine HCl 4% (40 mg/mL) and epinephrine 1:100,000 (as epinephrine bitartrate 0.018 mg/mL):
  - NDC 45146-110-02 (50 cartridges/box),
  - NDC 45146-110-01 (100 cartridges/box)

Both products are formulated with a 10% overage of epinephrine.

Storage and Handling
Store at 20° to 25°C (68° to 77°F); excursions permitted between 15° to 30°C (59° to 86°F) [See USP Controlled Room Temperature]. Protect from light. Do not freeze.

17 PATIENT COUNSELING INFORMATION

Loss of Sensation and Muscle Function

- Inform patients in advance of the possibility of temporary loss of sensation and muscle function following infiltration and nerve block injections [see Adverse Reactions (6.2)].
- Instruct patients not to eat or drink until normal sensation returns.

Methemoglobinemia

• Inform patients that use of local anesthetics may cause methemoglobinemia, a serious condition that must be treated promptly. Advise patients or caregivers to seek immediate medical attention if they or someone in their care experience the following signs or symptoms: pale, gray, or blue colored skin (cyanosis); headache; rapid heart rate; shortness of breath; lightheadedness; or fatigue.

Manufactured in Italy by:
Pierrel S.p.A. - Strada Statale Appia 46/48 - 81043

Capua (CE), Italy

Revised: 11/2018

00710723-02

PACKAGE LABEL

Package Label - Principal Display Panel – Orabloc® (Articaine Hydrochloride 4% and Epinephrine 1:100,000) Injection Cartridge Label

PACKAGE LABEL

Package Label - Principal Display Panel – Orabloc® (Articaine Hydrochloride 4% and Epinephrine 1:100,000) Injection Carton Label

PACKAGE LABEL

Package Label - Principal Display Panel – Orabloc® (Articaine Hydrochloride 4% and Epinephrine 1:200,000) Injection Cartridge Label

PACKAGE LABEL

Package Label - Principal Display Panel – Orabloc® (Articaine Hydrochloride 4% and Epinephrine 1:200,000) Injection Carton Label